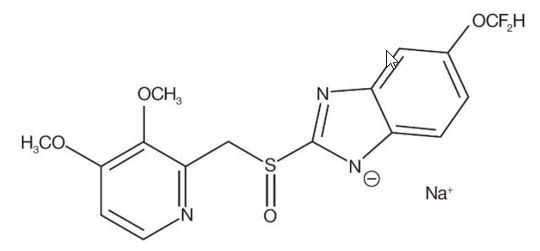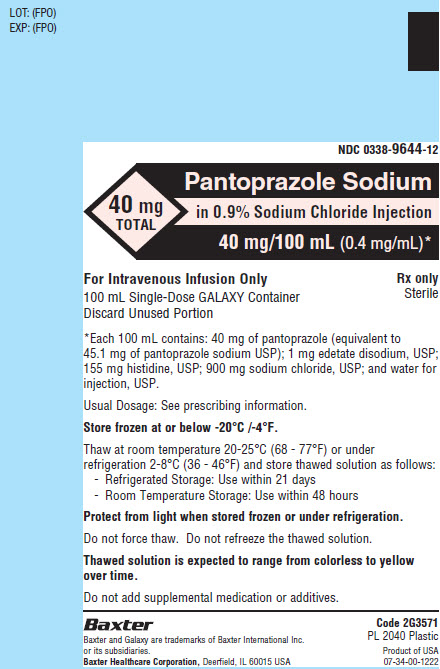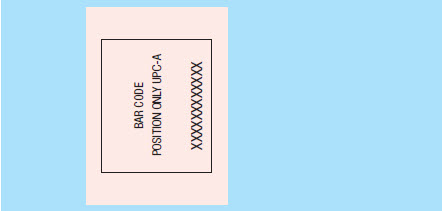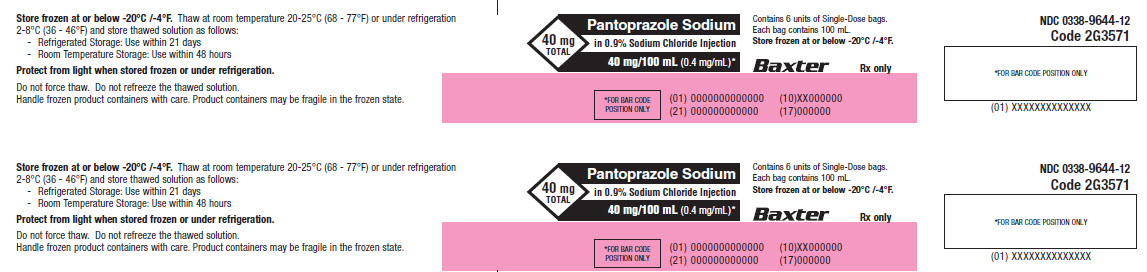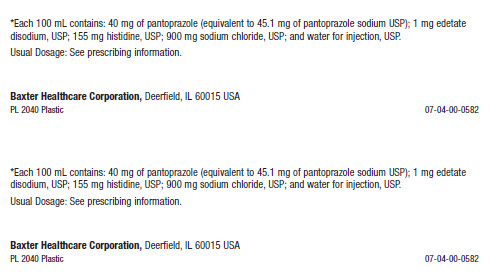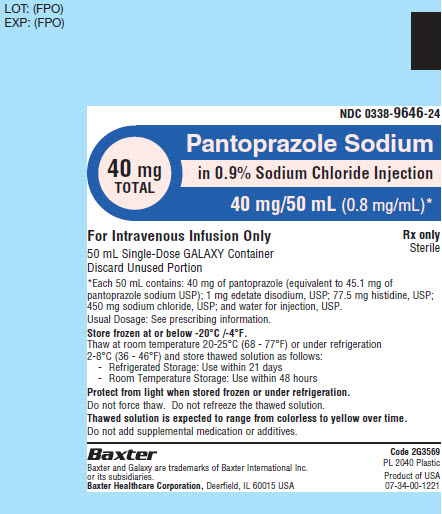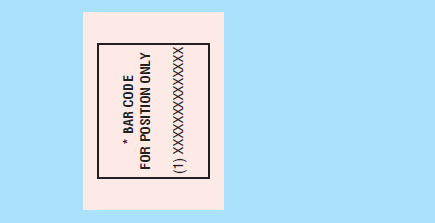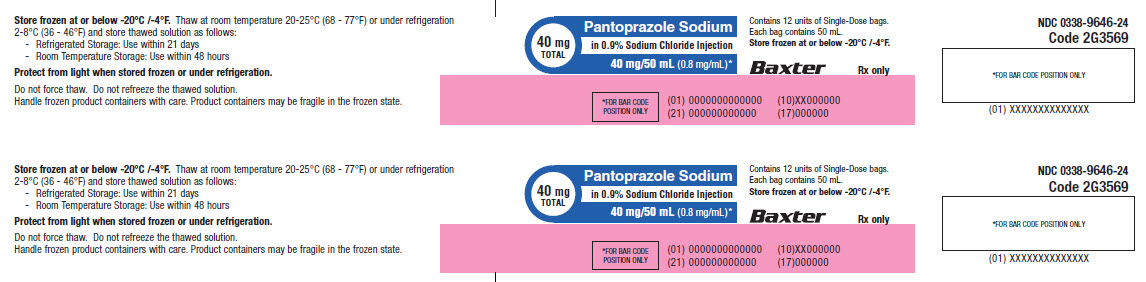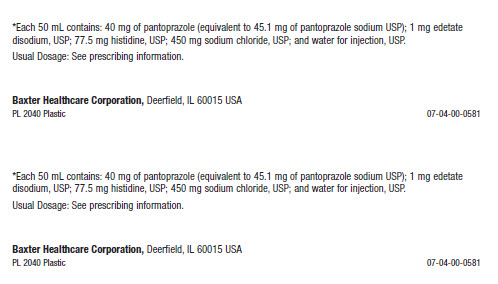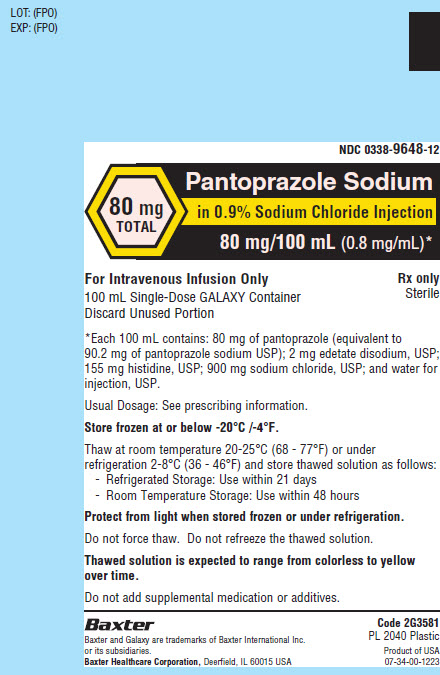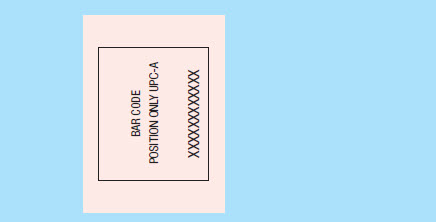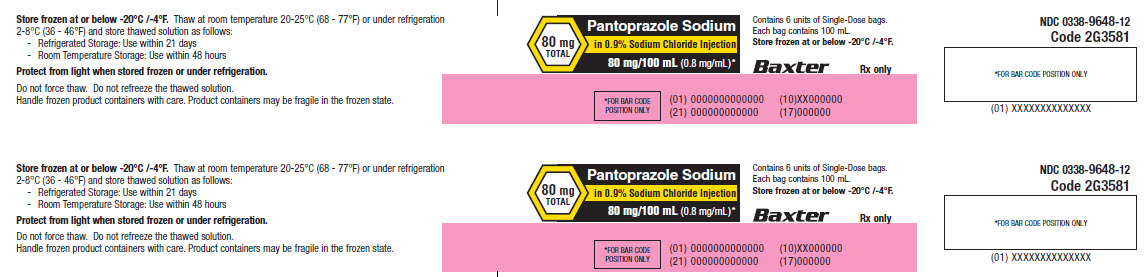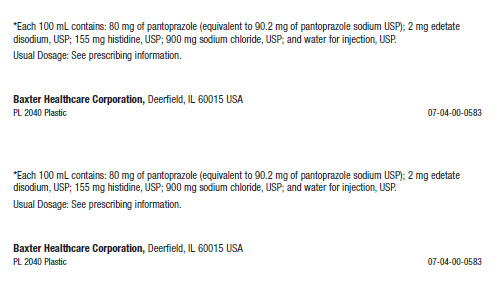 DRUG LABEL: PANTOPRAZOLE SODIUM
NDC: 0338-9644 | Form: INJECTION, SOLUTION
Manufacturer: Baxter Healthcare Corporation
Category: prescription | Type: HUMAN PRESCRIPTION DRUG LABEL
Date: 20240214

ACTIVE INGREDIENTS: PANTOPRAZOLE SODIUM 40 mg/100 mL
INACTIVE INGREDIENTS: EDETATE DISODIUM 1 mg/100 mL; HISTIDINE 155 mg/100 mL; SODIUM CHLORIDE 900 mg/100 mL; WATER

HIGHLIGHTS OF PRESCRIBING INFORMATION

These highlights do not include all the information needed to use PANTOPRAZOLE SODIUM IN 0.9% SODIUM CHLORIDE INJECTION safely and effectively. See full prescribing information for PANTOPRAZOLE SODIUM IN 0.9% SODIUM CHLORIDE INJECTION.
PANTOPRAZOLE SODIUM IN SODIUM CHLORIDE injection, for intravenous use
Initial U.S. Approval: 2000

1 INDICATIONS AND USAGE

Pantoprazole sodium is a proton pump inhibitor (PPI) indicated in adults for the following:

- Short-term treatment (7 to 10 days) of gastroesophageal reflux disease (GERD) associated with a history of Erosive Esophagitis (EE). (1.1)
- Pathological hypersecretion conditions including Zollinger-Ellison (ZE) Syndrome. (1.2)

2 DOSAGE AND ADMINISTRATION

GERD Associated with EE (2.1)

- The recommended adult dosage is 40 mg given once daily by intravenous infusion for 7 to 10 days. (2.1)

Pathological Hypersecretion Conditions, Including ZE Syndrome (2.2):

- The recommended adult dosage is 80 mg administered every 12 hours by intravenous infusion. For information on how to adjust dosing for individual patient needs, see the full prescribing information.

Administration (2.3):

- Only for intravenous infusion.
- The intravenous infusion should be administered over 15 minutes.

3 DOSAGE FORMS AND STRENGTHS

Injection: Pantoprazole sodium in 0.9% sodium chloride injection as available in 40 mg in 100 mL, 40 mg in 50 mL, and 80 mg in 100 mL single-dose Galaxy container. (3)

4 CONTRAINDICATIONS

- Patients with a known hypersensitivity to any component of the formulation or to substituted benzimidazoles. (4)
- Patients receiving rilpivirine-containing products. (4,7)

5 WARNINGS AND PRECAUTIONS

- Gastric Malignancy: In adults, symptomatic response to therapy with pantoprazole sodium in 0.9% sodium chloride injection does not preclude the presence of gastric malignancy.
  Consider additional follow-up and diagnostic testing. (5.1)
- Injection Site Reactions: Thrombophlebitis is associated with the administration of intravenous pantoprazole. (5.2)
- Potential Exacerbation of Zinc Deficiency: Consider zinc supplementation in patients who are prone to zinc deficiency. Caution should be used when other EDTA containing products are also co-administered intravenously. (5.3)
- Acute Tubulointerstitial Nephritis: Discontinue treatment and evaluate patients. (5.4)
- Clostridium difficile-Associated Diarrhea: PPI therapy may be associated with increased risk. (5.5)
- Bone Fracture: Long term and multiple daily dose PPI therapy may be associated with an increased risk for osteoporosis-related fractures of the hip, wrist or spine. (5.6)
- Severe Cutaneous Adverse Reactions: Discontinue at the first signs or symptoms of severe cutaneous adverse reactions or other signs of hypersensitivity and consider further evaluation. (5.7)
- Cutaneous and Systemic Lupus Erythematosus: Mostly cutaneous; new onset or exacerbation of existing disease; discontinue pantoprazole sodium in 0.9% sodium chloride injection and refer to specialist for evaluation. (5.8)
- Hepatic Effects: Elevations of transaminases observed. (5.9)
- Hypomagnesemia and Mineral Metabolism: Reported rarely with prolonged treatment with PPIs. (5.10)
- Fundic Gland Polyps: Risk increases with long-term use, especially beyond one year. Use the shortest duration of therapy. (5.11)

6 ADVERSE REACTIONS

Most common adverse reactions (>2%) are: headache, diarrhea, nausea, abdominal pain, vomiting, flatulence, dizziness, and arthralgia. (6.1)

To report SUSPECTED ADVERSE REACTIONS, contact Baxter Healthcare Corporation at 1-866-888-2472 or FDA at 1-800-FDA-1088 or www.fda.gov/medwatch.

7 DRUG INTERACTIONS

See the full prescribing information for a list of clinically important drug interactions. (7)

8 USE IN SPECIFIC POPULATIONS

Pregnancy: Based on animal data, may cause fetal harm. (8.1)

FULL PRESCRIBING INFORMATION

1 INDICATIONS AND USAGE

1.1 Gastroesophageal Reflux Disease Associated with a History of Erosive Esophagitis

Pantoprazole sodium in 0.9% sodium chloride injection is indicated for short-term treatment (7 to 10 days) of adult patients with gastroesophageal reflux disease (GERD) and a history of erosive esophagitis (EE).

Safety and efficacy of pantoprazole sodium in 0.9% sodium chloride injection as a treatment of patients with GERD and a history of EE for more than 10 days have not been demonstrated.

1.2 Pathological Hypersecretion Including Zollinger-Ellison Syndrome

Pantoprazole sodium in 0.9% sodium chloride injection is indicated for the treatment of pathological hypersecretory conditions including Zollinger-Ellison (ZE) Syndrome in adults.

2 DOSAGE AND ADMINISTRATION

2.1 Dosage for Gastroesophageal Reflux Disease Associated With a History of Erosive Esophagitis

The recommended adult dosage of pantoprazole sodium in 0.9% sodium chloride injection is 40 mg given once daily by intravenous infusion for 7 to 10 days.

Discontinue treatment with pantoprazole sodium in 0.9% sodium chloride injection as soon as the patient is able to receive treatment with pantoprazole delayed-release tablets or oral suspension.

Data on the safe and effective dosing for conditions other than those described [see Indications and Usage (1)] such as life-threatening upper gastrointestinal bleeds, are not available. Pantoprazole sodium in 0.9% sodium chloride injection 40 mg once daily does not raise gastric pH to levels sufficient to contribute to the treatment of such life-threatening conditions.

2.2 Dosage for Pathological Hypersecretion Including Zollinger-Ellison Syndrome

The recommended adult dosage of pantoprazole sodium in 0.9% sodium chloride injection is 80 mg intravenously every 12 hours. The frequency of dosing can be adjusted to individual patient needs based on acid output measurements. In those patients who need a higher dosage, 80 mg intravenously every 8 hours is expected to maintain acid output below 10 mEq/h. Daily doses higher than 240 mg or administered for more than 6 days have not been studied [see Clinical Studies (14)]. Transition from oral to intravenous and from intravenous to oral formulations of gastric acid inhibitors should be performed in such a manner to ensure continuity of effect of suppression of acid secretion. Patients with ZE Syndrome may be vulnerable to serious clinical complications of increased acid production even after a short period of loss of effective inhibition.

2.3 Preparation and Administration Instructions

Only for intravenous infusion over 15 minutes; other parenteral routes of administration and infusion rates are not recommended.

Fifteen Minute Infusion

1. Thaw frozen container at room temperature 20-25°C (68 - 77°F) or under refrigeration 2-8°C (36 - 46°F). Product should not be thawed by immersion in water baths or by microwave irradiation. Do not force thaw.
2. No further dilution is necessary.
3. Check for minute leaks by squeezing container firmly. If leaks are detected, discard solution as sterility may be impaired.
4. Do not add supplementary medication.
5. Inspect thawed pantoprazole sodium in 0.9% sodium chloride solution visually for particulate matter prior to and during administration. Thawed solution is expected to range from colorless to yellow over time..
6. Administer intravenously over a period of approximately 15 minutes.

Storage

Thawed solution is stable for 21 days under refrigeration 2-8°C (36 - 46°F) or 48 hours at room temperature 20-25°C (68 - 77°F). Protect from light when stored under refrigeration.

Do not refreeze the thawed solution.

2.4 Compatibility Information

- Administer pantoprazole sodium in 0.9% sodium chloride injection intravenously through a dedicated line or through a Y-site.
- Flush the intravenous line before and after administration of pantoprazole sodium in 0.9% sodium chloride injection with either 5% Dextrose Injection, USP, 0.9% Sodium Chloride Injection, USP, or Lactated Ringer’s Injection, USP.
- When administered through a Y-site, pantoprazole sodium in 0.9% sodium chloride injection is compatible with the following solutions: 5% Dextrose Injection, USP, 0.9% Sodium Chloride Injection, USP, or Lactated Ringer’s Injection, USP.
- Midazolam HCl has been shown to be incompatible with Y-site administration of pantoprazole sodium injection
- Pantoprazole sodium injection may not be compatible with products containing zinc [see Warnings and Precautions (5.3)].
- When pantoprazole sodium in 0.9% sodium chloride injection is administered through a Y-site, immediately stop use if precipitation or discoloration occurs.

3 DOSAGE FORMS AND STRENGTHS

Injection: Pantoprazole sodium in 0.9% sodium chloride injection is available in a ready to use single-dose GALAXY container supplied as a frozen, premixed, iso-osmotic, sterile, nonpyrogenic solution as follows:

- 40 mg/100 mL (0.4 mg/mL), each 100 mL contains 40 mg of pantoprazole (equivalent to 45.1 mg of pantoprazole sodium USP)
- 40 mg/50 mL (0.8 mg/mL) , each 50 mL contains 40 mg of pantoprazole (equivalent to 45.1 mg of pantoprazole sodium USP)
- 80 mg/100 mL (0.8 mg/mL) , each 100 mL contains 80 mg of pantoprazole (equivalent to 90.2 mg of pantoprazole sodium USP)

4 CONTRAINDICATIONS

- Pantoprazole sodium in 0.9% sodium chloride injection is contraindicated in patients with known hypersensitivity reactions including anaphylaxis to the formulation or any substituted benzimidazole. Hypersensitivity reactions may include anaphylaxis, anaphylactic shock, angioedema, bronchospasm, acute tubulointerstitial nephritis, and urticaria [see Warnings and Precautions (5.2, 5.4), Adverse Reactions (6)].
- Proton pump inhibitors (PPIs), including pantoprazole sodium in 0.9% sodium chloride injection, are contraindicated in patients receiving rilpivirine-containing products [see Drug Interactions (7)].

5 WARNINGS AND PRECAUTIONS

5.1 Presence of Gastric Malignancy

In adults, symptomatic response to therapy with pantoprazole sodium in 0.9% sodium chloride injection does not preclude the presence of gastric malignancy. Consider additional follow-up and diagnostic testing in adult patients who have a suboptimal response or an early symptomatic relapse after completing treatment with a PPI. In older patients, also consider an endoscopy.

5.2 Injection Site Reactions

Thrombophlebitis was associated with the administration of pantoprazole sodium injection.

5.3 Potential for Exacerbation of Zinc Deficiency

Pantoprazole sodium in 0.9% sodium chloride injection contains edetate disodium (the salt form of EDTA), a chelator of metal ions including zinc. Therefore, zinc supplementation should be considered in patients treated with pantoprazole sodium in 0.9% sodium chloride injection who are prone to zinc deficiency. Caution should be used when other EDTA containing products are also co-administered intravenously [see Dosage and Administration (2.4)].

5.4 Acute Tubulointerstitial Nephritis

Acute tubulointerstitial nephritis (TIN) has been observed in patients taking PPIs and may occur at any point during PPI therapy. Patients may present with varying signs and symptoms from symptomatic hypersensitivity reactions to non-specific symptoms of decreased renal function (e.g., malaise, nausea, anorexia). In reported case series, some patients were diagnosed on biopsy and in the absence of extra-renal manifestations (e.g., fever, rash or arthralgia). Discontinue pantoprazole sodium in 0.9% sodium chloride injection and evaluate patients with suspected acute TIN [see Contraindications (4)].

5.5 Clostridium difficile-Associated Diarrhea

Published observational studies suggest that PPI therapy like pantoprazole sodium in 0.9% sodium chloride injection may be associated with an increased risk of Clostridium difficile associated diarrhea, especially in hospitalized patients. This diagnosis should be considered for diarrhea that does not improve [see Adverse Reactions (6.2)].

Patients should use the lowest dose and shortest duration of PPI therapy appropriate to the condition being treated.

5.6 Bone Fracture

Several published observational studies suggest that PPI therapy may be associated with an increased risk for osteoporosis-related fractures of the hip, wrist, or spine. The risk of fracture was increased in patients who received high-dose, defined as multiple daily doses, and long-term PPI therapy (a year or longer). Patients should use the lowest dose and shortest duration of PPI therapy appropriate to the condition being treated. Patients at risk for osteoporosis-related fractures should be managed according to established treatment guidelines [see Dosage and Administration (2.1, 2.2), Adverse Reactions (6)].

5.7 Severe Cutaneous Adverse Reactions

Severe cutaneous adverse reactions, including erythema multiforme, Stevens-Johnson syndrome (SJS), toxic epidermal necrolysis (TEN), drug reaction with eosinophilia and systemic symptoms (DRESS), and acute generalized exanthematous pustulosis (AGEP) have been reported in association with the use of PPIs [see Adverse Reactions (6.2)]. Discontinue pantoprazole sodium in 0.9% sodium chloride injection at the first signs or symptoms of severe cutaneous adverse reactions or other signs of hypersensitivity and consider further evaluation.

5.8 Cutaneous and Systemic Lupus Erythematosus

Cutaneous lupus erythematosus (CLE) and systemic lupus erythematosus (SLE) have been reported in patients taking PPIs, including pantoprazole sodium. These events have occurred as both new onset and an exacerbation of existing autoimmune disease. The majority of PPI-induced lupus erythematous cases were CLE.

The most common form of CLE reported in patients treated with PPIs was subacute CLE (SCLE) and occurred within weeks to years after continuous drug therapy in patients ranging from infants to the elderly. Generally, histological findings were observed without organ involvement.

Systemic lupus erythematosus (SLE) is less commonly reported than CLE in patients receiving PPIs. PPI associated SLE is usually milder than non-drug induced SLE. Onset of SLE typically occurred within days to years after initiating treatment primarily in patients ranging from young adults to the elderly. The majority of patients presented with rash; however, arthralgia and cytopenia were also reported.

Avoid administration of PPIs for longer than medically indicated. If signs or symptoms consistent with CLE or SLE are noted in patients receiving pantoprazole sodium in 0.9% sodium chloride injection, discontinue the drug and refer the patient to the appropriate specialist for evaluation. Most patients improve with discontinuation of the PPI alone in 4 to 12 weeks. Serological testing (e.g., ANA) may be positive and elevated serological test results may take longer to resolve than clinical manifestations.

5.9 Hepatic Effects

Mild, transient transaminase elevations have been observed in clinical studies. The clinical significance of this finding in a large population of subjects administered pantoprazole sodium injection is unknown [see Adverse Reactions (6)].

5.10 Hypomagnesemia and Mineral Metabolism

Hypomagnesemia, symptomatic and asymptomatic, has been reported rarely in patients treated with PPIs for at least three months, and in most cases after a year of therapy. Serious adverse events include tetany, arrhythmias, and seizures. Hypomagnesemia may lead to hypocalcemia and/or hypokalemia and may exacerbate underlying hypocalcemia in at-risk patients. In most patients, treatment of hypomagnesemia required magnesium replacement and discontinuation of the PPI.

For patients expected to be on prolonged treatment or who take PPIs with medications such as digoxin or drugs that may cause hypomagnesemia (e.g., diuretics), health care professionals may consider monitoring magnesium levels prior to initiation of PPI treatment and periodically [see Adverse Reactions (6.2)].

Consider monitoring magnesium and calcium levels prior to initiation of pantoprazole sodium in 0.9% sodium chloride injection and periodically while on treatment in patients with a preexisting risk of hypocalcemia (e.g., hypoparathyroidism). Supplement with magnesium and/or calcium as necessary. If hypocalcemia is refractory to treatment, consider discontinuing the PPI.

5.11 Fundic Gland Polyps

PPI use is associated with an increased risk of fundic gland polyps that increases with long-term use, especially beyond one year. Most PPI users who developed fundic gland polyps were asymptomatic and fundic gland polyps were identified incidentally on endoscopy. Use the shortest duration of PPI therapy appropriate to the condition being treated.

5.12 Interference with Investigations for Neuroendocrine Tumors

Serum chromogranin A (CgA) levels increase secondary to drug-induced decreases in gastric acidity. The increased CgA level may cause false positive results in diagnostic investigations for neuroendocrine tumors. Healthcare providers should temporarily stop pantoprazole sodium injection treatment at least 14 days before assessing CgA levels and consider repeating the test if initial CgA levels are high. If serial tests are performed (e.g., for monitoring), the same commercial laboratory should be used for testing, as reference ranges between tests may vary [see Clinical Pharmacology (12.2)].

5.13 Interference with Urine Screen for THC

Pantoprazole sodium may produce false-positive urine screen for THC (tetrahydrocannabinol) [see Drug Interactions (7)].

5.14 Concomitant Use of Pantoprazole in 0.9% Sodium Injection with Methotrexate

Literature suggests that concomitant use of PPIs with methotrexate (primarily at high dose; see methotrexate prescribing information) may elevate and prolong serum levels of methotrexate and/or its metabolite, possibly leading to methotrexate toxicities. In high-dose methotrexate administration, a temporary withdrawal of the PPI may be considered in some patients [see Drug Interactions (7)].

6 ADVERSE REACTIONS

The following serious adverse reactions are described below and elsewhere in labeling:

- Injection Site Reactions [see Warnings and Precautions (5.2)]
- Potential for Exacerbation of Zinc Deficiency [see Warnings and Precautions (5.3)]
- Acute Tubulointerstitial Nephritis [see Warnings and Precautions (5.4)]
- Clostridium difficile-Associated Diarrhea [see Warnings and Precautions (5.5)]
- Bone Fracture [see Warnings and Precautions (5.6)]
- Severe Cutaneous Adverse Reactions [see Warnings and Precautions (5.7)]
- Cutaneous and Systemic Lupus Erythematosus [see Warnings and Precautions (5.8)]
- Hepatic Effects [see Warnings and Precautions (5.9)]
- Hypomagnesemia and Mineral Metabolism [see Warnings and Precautions (5.10)]
- Fundic Gland Polyps [see Warnings and Precautions (5.11)]

6.1 Clinical Trials Experience

Because clinical trials are conducted under widely varying conditions, adverse reaction rates observed in the clinical trials of a drug cannot be directly compared to rates in the clinical trials of another drug and may not reflect the rates observed in clinical practice.

Worldwide, approximately 80,500 patients have been treated with pantoprazole in clinical trials involving various dosages and duration of treatment.

Gastroesophageal Reflux Disease (GERD)

Safety in nine randomized comparative US clinical trials in patients with GERD included 1,473 patients on oral pantoprazole sodium (20 mg or 40 mg), 299 patients on an H2-receptor antagonist, 46 patients on another PPI, and 82 patients on placebo. The most frequently occurring adverse reactions are listed in Table 1.

The number of patients treated in comparative studies with pantoprazole sodium injection is limited; however, the adverse reactions seen were similar to those seen in the oral studies. Thrombophlebitis was the only new adverse reaction identified with pantoprazole sodium injection.

Table 1. Adverse Reactions Reported in Clinical Trials of Adult Patients with GERD at a Frequency of > 2%
 | Oral Pantoprazole Sodium (n=1473) % | Comparators (n=345) % | Placebo (n=82) %
Headache | 12.2 | 12.8 | 8.5
Diarrhea | 8.8 | 9.6 | 4.9
Nausea | 7.0 | 5.2 | 9.8
Abdominal pain | 6.2 | 4.1 | 6.1
Vomiting | 4.3 | 3.5 | 2.4
Flatulence | 3.9 | 2.9 | 3.7
Dizziness | 3.0 | 2.9 | 1.2
Arthralgia | 2.8 | 1.4 | 1.2

Additional adverse reactions that were reported for oral pantoprazole sodium in US clinical trials with a frequency of ≤2% are listed below by body system:

Body as a Whole: allergic reaction, fever, photosensitivity reaction, facial edema, thrombophlebitis (I.V. only)
Gastrointestinal: constipation, dry mouth, hepatitis
Hematologic: leukopenia (reported in ex-US clinical trials only), thrombocytopenia
Metabolic/Nutritional: elevated CPK (creatine phosphokinase), generalized edema, elevated triglycerides, liver function tests abnormal
Musculoskeletal: myalgia
Nervous: depression, vertigo
Skin and Appendages: urticaria, rash, pruritus
Special Senses: blurred vision

Zollinger-Ellison (ZE) Syndrome

In clinical studies of ZE Syndrome, adverse reactions reported in 35 patients administered pantoprazole sodium injection doses of 80 mg to 240 mg per day for up to 2 years were similar to those reported in adult patients with GERD.

6.2 Postmarketing Experience

The following adverse reactions have been identified during postapproval use of oral pantoprazole sodium and pantoprazole sodium injection. Because these reactions are reported voluntarily from a population of uncertain size, it is not always possible to reliably estimate their frequency or establish a causal relationship to drug exposure.

These adverse reactions are listed below by body system:

General Disorders and Administration Conditions: asthenia, fatigue, malaise
Immune System Disorders: anaphylaxis (including anaphylactic shock), systemic lupus erythematosus
Investigations: weight changes
Skin and Subcutaneous Tissue Disorders: severe dermatologic reactions (some fatal), including erythema multiforme, SJS/TEN, DRESS, AGEP, angioedema (Quincke’s edema) and cutaneous lupus erythematosus
Musculoskeletal Disorders: rhabdomyolysis, bone fracture
Renal and Genitourinary Disorders: acute tubulointerstitial nephritis, erectile dysfunction
Hepatobiliary Disorders: hepatocellular damage leading to jaundice and hepatic failure
Psychiatric Disorder: hallucinations, confusion, insomnia, somnolence
Metabolism and Nutritional Disorders: hyponatremia, hypomagnesemia, hypocalcemia, hypokalemia, hyponatremia
Infections and Infestations: Clostridium difficile associated diarrhea
Hematologic: pancytopenia, agranulocytosis
Nervous: ageusia, dysgeusia
Gastrointestinal Disorders: fundic gland polyps

7 DRUG INTERACTIONS

Table 2 includes drugs with clinically important drug interactions and interaction with diagnostics when administered concomitantly with pantoprazole sodium injection and instructions for preventing or managing them.

Consult the labeling of concomitantly used drugs to obtain further information about interactions with PPIs.

Table 2. Clinically Relevant Interactions Affecting Drugs Co-Administered with Pantoprazole Sodium in 0.9% Sodium Chloride Injection and Interaction with Diagnostics
Antiretrovirals
Clinical Impact: | The effect of PPIs on antiretroviral drugs is variable. The clinical importance and the mechanisms behind these interactions are not always known.; - Decreased exposure of some antiretroviral drugs (e.g., rilpivirine atazanavir, and nelfinavir) when used concomitantly with pantoprazole may reduce antiviral effect and promote the development of drug resistance. - Increased exposure of other antiretroviral drugs (e.g., saquinavir) when used concomitantly with pantoprazole may increase toxicity of the antiretroviral drugs. - There are other antiretroviral drugs which do not result in clinically relevant interactions with pantoprazole.
Intervention: | Rilpivirine-containing products: Concomitant use with pantoprazole sodium in 0.9% sodium chloride injection is contraindicated [see Contraindications (4)]. See prescribing information.; Atazanavir: See prescribing information for atazanavir for dosing information.; Nelfinavir: Avoid concomitant use with pantoprazole sodium in 0.9% sodium chloride injection See prescribing information for nelfinavir.; Saquinavir: See the prescribing information for saquinavir and monitor for potential saquinavir toxicities.; Other antiretrovirals: See prescribing information.
Warfarin
Clinical Impact: | Increased INR and prothrombin time in patients receiving PPIs, including pantoprazole, and warfarin concomitantly. Increases in INR and prothrombin time may lead to abnormal bleeding and even death.
Intervention: | Monitor INR and prothrombin time. Dose adjustment of warfarin may be needed to maintain target INR range. See prescribing information for warfarin.
Clopidogrel
Clinical Impact: | Concomitant administration of pantoprazole and clopidogrel in healthy subjects had no clinically important effect on exposure to the active metabolite of clopidogrel or clopidogrel-induced platelet inhibition [see Clinical Pharmacology (12.3)].
Intervention: | No dose adjustment of clopidogrel is necessary when administered with an approved dose of pantoprazole sodium in 0.9% sodium chloride injection.
Methotrexate
Clinical Impact: | Concomitant use of PPIs with methotrexate (primarily at high dose) may elevate and prolong serum concentrations of methotrexate and/or its metabolite hydroxymethotrexate, possibly leading to methotrexate toxicities. No formal drug interaction studies of high-dose methotrexate with PPIs have been conducted [see Warnings and Precautions (5.14)].
Intervention: | A temporary withdrawal of pantoprazole sodium in 0.9% sodium chloride injection may be considered in some patients receiving high-dose methotrexate.
Drugs Dependent on Gastric pH for Absorption (e.g., iron salts, erlotinib, dasatinib, nilotinib, mycophenolate mofetil, ketoconazole/itraconazole)
Clinical Impact: | Pantoprazole can reduce the absorption of other drugs due to its effect on reducing intragastric acidity.
Intervention: | Mycophenolate mofetil (MMF): Co-administration of pantoprazole sodium in healthy subjects and in transplant patients receiving MMF has been reported to reduce the exposure to the active metabolite, mycophenolic acid (MPA), possibly due to a decrease in MMF solubility at an increased gastric pH [see Clinical Pharmacology (12.3)]. The clinical relevance of reduced MPA exposure on organ rejection has not been established in transplant patients receiving pantoprazole sodium injection and MMF. Use pantoprazole sodium in 0.9% sodium chloride injection with caution in transplant patients receiving MMF.; See the prescribing information for other drugs dependent on gastric pH for absorption.
Interactions with Investigations of Neuroendocrine Tumors
Clinical Impact: | CgA levels increase secondary to PPI-induced decreases in gastric acidity. The increased CgA level may cause false positive results in diagnostic investigations for neuroendocrine tumors [see Warnings and Precautions (5.12), Clinical Pharmacology (12.2)].
Intervention: | Temporarily stop pantoprazole sodium in 0.9% sodium chloride injection treatment at least 14 days before assessing CgA levels and consider repeating the test if initial CgA levels are high. If serial tests are performed (e.g. for monitoring), the same commercial laboratory should be used for testing, as reference ranges between tests may vary.
False Positive Urine Tests for THC
Clinical Impact: | There have been reports of false positive urine screening tests for tetrahydrocannabinol (THC) in patients receiving PPIs [see Warnings and Precautions (5.13)].
Intervention: | An alternative confirmatory method should be considered to verify positive results.

8 USE IN SPECIFIC POPULATIONS

8.1 Pregnancy

Risk Summary

Available data from published observational studies did not demonstrate an association of major malformations or other adverse pregnancy outcomes with pantoprazole.

In animal reproduction studies, no evidence of adverse development outcomes was observed with pantoprazole. Reproduction studies have been performed in rats at intravenous doses up to 20 mg/kg/day (4 times the recommended human dose) and rabbits at intravenous doses up to 15 mg/kg/day (6 times the recommended human dose) with administration of pantoprazole during organogenesis in pregnant animals and have revealed no evidence of harm to the fetus due to pantoprazole in this study (see Data).

A pre-and post-natal development toxicity study in rats with additional endpoints to evaluate the effect on bone development was performed with pantoprazole sodium. Oral pantoprazole doses of 5, 15, and 30 mg/kg/day (approximately 1, 3, and 6 times the human dose of 40 mg/day) were administered to pregnant females from gestation day (GD) 6 through lactation day (LD) 21. Changes in bone morphology were observed in pups exposed to pantoprazole in utero and through milk during the period of lactation as well as by oral dosing from postnatal day (PND) 4 through PND 21 [see Use in Specific Populations (8.4)]. There were no drug-related findings in maternal animals. Advise pregnant women of the potential risk of fetal harm.

The estimated background risk of major birth defects and miscarriage for the indicated population is unknown. All pregnancies have a background risk of birth defect, loss or other adverse outcomes. In the U.S. general population, the estimated background risk of major birth defects and miscarriage in the clinically recognized pregnancies is 2 to 4% and 15 to 20%, respectively.

Data

Human Data

Available data from published observational studies failed to demonstrate an association of adverse pregnancy-related outcomes and pantoprazole use. Methodological limitations of these observational studies cannot definitely establish or exclude any drug-associated risk during pregnancy. In a prospective study by the European Network of Teratology Information Services, outcomes from a group of 53 pregnant women administered median daily doses of 40 mg pantoprazole were compared to a control group of 868 pregnant women who did not take any proton pump inhibitors (PPIs). There was no difference in the rate of major malformations between women exposed to PPIs and the control group, corresponding to a Relative Risk (RR)=0.55, [95% Confidence Interval (CI) 0.08-3.95]. In a population-based retrospective cohort study covering all live births in Denmark from 1996 to 2008, there was no significant increase in major birth defects during analysis of first trimester exposure to pantoprazole in 549 live births. A meta-analysis that compared 1,530 pregnant women exposed to PPIs in at least the first trimester with 133,410 unexposed pregnant women showed no significant increases in risk for congenital malformations or spontaneous abortion with exposure to PPIs (for major malformations OR=1.12 ([95% CI 0.86-1.45] and for spontaneous abortions OR=1.29 [95% CI 0.84-1.97]).

Animal Data

Reproduction studies have been performed in rats at intravenous pantoprazole doses up to 20 mg/kg/day (4 times the recommended human dose based on body surface area) and rabbits at intravenous doses up to 15 mg/kg/day (6 times the recommended human dose based on body surface area) with administration of pantoprazole sodium during organogenesis in pregnant animals and have revealed no evidence of impaired fertility or harm to the fetus due to pantoprazole.

A pre- and post-natal development toxicity study in rats with additional endpoints to evaluate the effect on bone development was performed with pantoprazole sodium. Oral pantoprazole doses of 5, 15, and 30 mg/kg/day (approximately 1, 3, and 6 times the human dose of 40 mg/day on a body surface area basis) were administered to pregnant females from gestation day (GD) 6 through lactation day (LD) 21. On postnatal day (PND 4) through PND 21, the pups were administered oral doses at 5, 15, and 30 mg/kg/day (approximately 1, 2.3, and 3.2 times the exposure (AUC) in humans at a dose of 40 mg). There were no drug-related findings in maternal animals. During the preweaning dosing phase (PND 4 to 21) of the pups, there were increased mortality and/or moribundity and decreased body weight and body weight gain at 5 mg/kg/day (approximately equal exposures (AUC) in humans receiving the 40 mg dose) and higher doses. On PND 21, decreased mean femur length and weight and changes in femur bone mass and geometry were observed in the offspring at 5 mg/kg/day (approximately equal exposures (AUC) in humans at the 40 mg dose) and higher doses. The femur findings included lower total area, bone mineral content and density, periosteal and endosteal circumference, and cross-sectional moment of inertia. There were no microscopic changes in the distal femur, proximal tibia, or stifle joints. Changes in bone parameters were partially reversible following a recovery period, with findings on PND 70 limited to lower femur metaphysis cortical/subcortical bone mineral density in female pups at 5 mg/kg/day (approximately equal exposures (AUC) in humans at the 40 mg dose) and higher doses.

8.2 Lactation

Risk Summary

Pantoprazole has been detected in breast milk of a nursing mother after a single 40 mg oral dose of pantoprazole. There were no effects on the breastfed infant (see Data). There are no data on pantoprazole effects on milk production.

The developmental and health benefits of breastfeeding should be considered along with the mother’s clinical need for pantoprazole sodium in 0.9% sodium chloride injection and any potential adverse effects on the breastfed child from pantoprazole or from the underlying maternal condition.

Data

The breast milk of a 42-year-old woman receiving 40 mg of oral pantoprazole, at 10 months postpartum, was studied for 24 hours, to demonstrate low levels of pantoprazole present in the breast milk. Pantoprazole was detectable in milk only 2 and 4 hours after the dose with milk levels of approximately 36 mcg/L and 24 mcg/L, respectively. A milk-to-plasma ratio of 0.022 was observed at 2 hours after drug administration. Pantoprazole was not detectable (<10 mcg/L) in milk at 6, 8 and 24 hours after the dose. The relative dose to the infant was estimated to be 7.3 mcg of pantoprazole, which is equivalent to 0.14% of the weight-adjusted maternal dose. No adverse events in the infant were reported by the mother.

8.4 Pediatric Use

The safety and effectiveness of pantoprazole sodium in 0.9% sodium chloride injection have not been established in pediatric patients.

Animal Toxicity Data

In a pre- and post-natal development toxicity study in rats, the pups were administered oral doses of pantoprazole at 5, 15, and 30 mg/kg/day on postnatal day (PND 4) through PND 21, in addition to lactational exposure through milk. On PND 21, decreased mean femur length and weight and changes in femur bone mass and geometry were observed in the offspring at 5 mg/kg/day and higher doses. Changes in bone parameters were partially reversible following a recovery period [see Use in Specific Populations (8.1)].

In neonatal/juvenile animals (rats and dogs) toxicities were similar to those observed in adult animals, including gastric alterations, decreases in red cell mass, increases in lipids, enzyme induction and hepatocellular hypertrophy. An increased incidence of eosinophilic chief cells in adult and neonatal/juvenile rats, and atrophy of chief cells in adult rats and in neonatal/juvenile dogs, was observed in the fundic mucosa of stomachs in repeated-dose studies. Full to partial recovery of these effects were noted in animals of both age groups following a recovery period.

8.5 Geriatric Use

Of 286 patients in clinical studies of intravenous pantoprazole sodium in patients with GERD and a history of EE, 86 (43%) were 65 years of age and over. No overall differences in safety or effectiveness were observed between these subjects and younger subjects, and other reported clinical experience with oral pantoprazole sodium has not identified differences in responses between the elderly and younger patients, but greater sensitivity of some older individuals cannot be ruled out.

10 OVERDOSAGE

Experience in patients taking very high doses of pantoprazole (greater than 240 mg) is limited. Adverse reactions seen in spontaneous reports of overdose generally reflect the known safety profile of pantoprazole.

Pantoprazole is not removed by hemodialysis. In case of overdose, treatment should be symptomatic and supportive.

Single intravenous doses of pantoprazole at 378, 230, and 266 mg/kg (38, 46, and 177 times the recommended human dose based on body surface area) were lethal to mice, rats and dogs, respectively. The symptoms of acute toxicity were hypoactivity, ataxia, hunched sitting, limb-splay, lateral position, segregation, absence of ear reflex, and tremor.

11 DESCRIPTION

The active ingredient in pantoprazole sodium in 0.9% sodium chloride injection, a PPI, is a substituted benzimidazole, sodium 5-(difluoromethoxy)-2-[[(3,4-dimethoxy-2-pyridinyl)methyl] sulfinyl]-1H-benzimidazole, a compound that inhibits gastric acid secretion. Its empirical formula is C16H14F2N3NaO4S, with a molecular weight of 405.4. The structural formula is:

Pantoprazole sodium is a white to off-white crystalline powder and is racemic. Pantoprazole has weakly basic and acidic properties. Pantoprazole sodium is freely soluble in water, very slightly soluble in phosphate buffer at pH 7.4, and practically insoluble in n-hexane. The stability of the compound in aqueous solution is pH-dependent. The rate of degradation increases with decreasing pH. The thawed solution of pantoprazole sodium in 0.9% sodium chloride injection is in the pH range 9.0 to 10.5.

Pantoprazole sodium in 0.9% sodium chloride injection is supplied for intravenous administration as a frozen, premixed, iso-osmotic, sterile, nonpyrogenic 50 mL or 100 mL single-dose GALAXY container in following presentations:

40 mg/100 mL (0.4 mg/mL): containing 40 mg of pantoprazole (equivalent to 45.1 mg of pantoprazole sodium USP); 1 mg edetate disodium, USP; 155 mg histidine, USP; 900 mg sodium chloride, USP;

40 mg/50 mL (0.8 mg/mL): containing 40 mg of pantoprazole (equivalent to 45.1 mg of pantoprazole sodium USP); 1 mg edetate disodium, USP; 77.5 mg histidine, USP; 450 mg sodium chloride, USP;

80 mg/100 mL (0.8 mg/mL): containing 80 mg of pantoprazole (equivalent to 90.2 mg of pantoprazole sodium USP); 2 mg edetate disodium, USP; 155 mg histidine, USP; 900 mg sodium chloride, USP;

Sodium hydroxide and/or hydrochloric acid may be used to adjust pH.

The solution is intended for intravenous use after thawing to room temperature. Thawed solution is expected to range from colorless to yellow over time.

12 CLINICAL PHARMACOLOGY

12.1 Mechanism of Action

Pantoprazole is a PPI that suppresses the final step in gastric acid production by covalently binding to the (H^+, K^+)-ATPase enzyme system at the secretory surface of the gastric parietal cell. This effect leads to inhibition of both basal and stimulated gastric acid secretion irrespective of the stimulus. The binding to the (H^+, K^+)-ATPase results in a duration of antisecretory effect that persists longer than 24 hours for all doses tested (20 mg to 120 mg).

12.2 Pharmacodynamics

Antisecretory Activity

The magnitude and time course for inhibition of pentagastrin-stimulated acid output (PSAO) by single doses (20 to 120 mg) of pantoprazole sodium injection were assessed in a single-dose, open-label, placebo-controlled, dose-response study. The results of this study are shown in Table 3. Healthy subjects received a continuous infusion for 25 hours of pentagastrin (PG) at 1 mcg/kg/h, a dose known to produce submaximal gastric acid secretion. The placebo group showed a sustained, continuous acid output for 25 hours, validating the reliability of the testing model. Pantoprazole sodium injection had an onset of antisecretory activity within 15 to 30 minutes of administration. Doses of 20 to 80 mg of pantoprazole sodium injection substantially reduced the 24-hour cumulative PSAO in a dose-dependent manner, despite a short plasma elimination half-life. Complete suppression of PSAO was achieved with 80 mg within approximately 2 hours and no further significant suppression was seen with 120 mg. The duration of action of pantoprazole sodium injection was 24 hours.

Table 3. Gastric Acid Output (mEq/hr, Mean ± SD) and Percent Inhibition [Compared to individual subject baseline prior to treatment with pantoprazole sodium injection. NA = not applicable.] (Mean ± SD) of Pentagastrin-Stimulated Acid Output Over 24 Hours Following a Single Dose of Pantoprazole Sodium Injection [Inhibition of gastric acid output and the percent inhibition of stimulated acid output in response to pantoprazole sodium injection may be higher after repeated doses.] in Healthy Subjects
Treatment Dose | 2 hours |  | 4 hours |  | 12 hours |  | 24 hours
Treatment Dose | Acid Output | % Inhibition | Acid Output | % Inhibition | Acid Output | % Inhibition | Acid Output | % Inhibition
0 mg (Placebo,; n=4) | 39 ± 21 | NA | 26 ± 14 | NA | 32 ± 20 | NA | 38 ± 24 | NA
20 mg (n=4-6) | 13 ± 18 | 47 ± 27 | 6 ± 8 | 83 ± 21 | 20 ± 20 | 54 ± 44 | 30 ± 23 | 45 ± 43
40 mg (n=8) | 5 ± 5 | 82 ± 11 | 4 ± 4 | 90 ± 11 | 11 ± 10 | 81 ± 13 | 16 ± 12 | 52 ± 36
80 mg (n=8) | 0.1 ± 0.2 | 96 ± 6 | 0.3 ± 0.4 | 99 ± 1 | 2 ± 2 | 90 ± 7 | 7 ± 4 | 63 ± 18

In one study of gastric pH in healthy subjects, pantoprazole sodium was administered orally (40 mg enteric coated tablets) or pantoprazole sodium injection (40 mg) once daily for 5 days and pH was measured for 24 hours following the fifth dose. The outcome measure was median percent of time that pH was ≥4 and the results were similar for intravenous and oral medications; however, the clinical significance of this parameter is unknown.

Serum Gastrin Effects

Serum gastrin concentrations were assessed in two placebo-controlled studies.

In a 5-day study of oral pantoprazole with 40 and 60 mg doses in healthy subjects, following the last dose on day 5, median 24-hour serum gastrin concentrations were elevated by 3- to 4-fold compared to placebo in both 40 and 60 mg dose groups. However, by 24 hours following the last dose, median serum gastrin concentrations for both groups returned to normal levels.

In another placebo-controlled, 7-day study of 40 mg intravenous or oral pantoprazole in patients with GERD and a history of EE, the mean serum gastrin concentration increased approximately 50% from baseline and as compared with placebo, but remained within the normal range.

During 6 days of repeated administration of pantoprazole sodium injection in patients with ZE Syndrome, consistent changes of serum gastrin concentrations from baseline were not observed.

Enterochromaffin-Like (ECL) Cell Effects

There are no data available on the effects of intravenous pantoprazole sodium on ECL cells.

In a nonclinical study in Sprague-Dawley rats, lifetime exposure (24 months) to oral pantoprazole at doses of 0.5 to 200 mg/kg/day resulted in dose-related increases in gastric ECL-cell proliferation and gastric neuroendocrine (NE)-cell tumors. Gastric NE-cell tumors in rats may result from chronic elevation of serum gastrin concentrations. The high density of ECL cells in the rat stomach makes this species highly susceptible to the proliferative effects of elevated gastrin concentrations produced by PPIs. However, there were no observed elevations in serum gastrin following the administration of oral pantoprazole at a dose of 0.5 mg/kg/day. In a separate study, a gastric NE-cell tumor without concomitant ECL-cell proliferative changes was observed in 1 female rat following 12 months of dosing with oral pantoprazole at 5 mg/kg/day and a 9 month off-dose recovery [see Nonclinical Toxicology (13.1)].

Endocrine Effects

In a clinical pharmacology study, pantoprazole 40 mg given orally once daily for 2 weeks had no effect on the levels of the following hormones: cortisol, testosterone, triiodothyronine (T3), thyroxine (T4), thyroid-stimulating hormone, thyronine-binding protein, parathyroid hormone, insulin, glucagon, renin, aldosterone, follicle-stimulating hormone, luteinizing hormone, prolactin and growth hormone.

In a 1-year study of GERD patients treated with pantoprazole 40 mg or 20 mg, there were no changes from baseline in overall levels of T3, T4, and TSH.

12.3 Pharmacokinetics

Pantoprazole peak serum concentration (Cmax) and area under the serum concentration-time curve (AUC) increase in a manner proportional to intravenous doses from 10 mg to 80 mg. Pantoprazole does not accumulate and its pharmacokinetics are unaltered with multiple daily dosing. Following the administration of pantoprazole sodium injection, the serum concentration of pantoprazole declines biexponentially with a terminal elimination half-life of approximately one hour. In CYP2C19 extensive metabolizers [see Clinical Pharmacology (12.5)] with normal liver function receiving a 40 mg dose of pantoprazole sodium injection. by constant rate over 15 minutes, the peak concentration (Cmax) is 5.52 ±1.42 mcg/mL and the total area under the plasma concentration versus time curve (AUC) is 5.4 ±1.5 mcg hr/mL. The total clearance is 7.6 to 14 L/h.

Distribution

The apparent volume of distribution of pantoprazole is approximately 11 to 23.6 L, distributing mainly in extracellular fluid. The serum protein binding of pantoprazole is about 98%, primarily to albumin.

Elimination

Metabolism

Pantoprazole is extensively metabolized in the liver through the cytochrome P450 (CYP) system. Pantoprazole metabolism is independent of the route of administration (intravenous or oral). The main metabolic pathway is demethylation, by CYP2C19, with subsequent sulfation; other metabolic pathways include oxidation by CYP3A4. There is no evidence that any of the pantoprazole metabolites have significant pharmacologic activity. CYP2C19 displays a known genetic polymorphism due to its deficiency in some sub-populations (e.g., 3% of Caucasians and African-Americans and 17 to 23% of Asians). Although these sub-populations of slow pantoprazole metabolizers have elimination half-life values from 3.5 to 10 hours, they still have minimal accumulation (23% or less) with once daily dosing.

Excretion

After administration of a single intravenous dose of ^14C-labeled pantoprazole sodium to healthy, extensive CYP2C19 metabolizers, approximately 71% of the dose was excreted in the urine with 18% excreted in the feces through biliary excretion. There was no renal excretion of unchanged pantoprazole.

Specific Populations

Geriatric Patients

After repeated intravenous administration in elderly subjects (65 to 76 years of age), the AUC and elimination half-life values of pantoprazole were similar to those observed in younger subjects.

Male and Female Patients

After oral administration there was a modest increase in the AUC and Cmax of pantoprazole in women compared to men. However, weight-normalized clearance values are similar in women and men.

Patients with Renal Impairment

In patients with severe renal impairment, pharmacokinetic parameters for pantoprazole were similar to those of healthy subjects.

Patients with Hepatic Impairment

In patients with mild to severe hepatic impairment (Child-Pugh Class A to C), maximum pantoprazole concentrations increased only slightly (1.5-fold) relative to healthy subjects when pantoprazole sodium was administered orally. Although serum half-life values increased to 7 to 9 hours and AUC values increased by 5 to 7-fold in hepatic-impaired patients, these increases were no greater than those observed in CYP2C19 poor metabolizers, where no dosage adjustment is warranted. These pharmacokinetic changes in hepatic-impaired patients result in minimal drug accumulation following once-daily, multiple-dose administration. Oral pantoprazole doses higher than 40 mg per day have not been studied in hepatically impaired patients.

Drug Interaction Studies

Effect of Other Drugs on Pantoprazole

Pantoprazole is metabolized mainly by CYP2C19 and to minor extents by CYPs 3A4, 2D6 and 2C9.

In in vivo drug-drug interaction studies with CYP2C19 substrates (diazepam [also a CYP3A4 substrate] and phenytoin [also a CYP3A4 inducer]), nifedipine, midazolam, and clarithromycin (CYP3A4 substrates), metoprolol (a CYP2D6 substrate), diclofenac, naproxen and piroxicam (CYP2C9 substrates) and theophylline (a CYP1A2 substrate) in healthy subjects, the pharmacokinetics of pantoprazole were not significantly altered.

Effect of Pantoprazole on Other Drugs

Clopidogrel

Clopidogrel is metabolized to its active metabolite in part by CYP2C19. In a crossover clinical study, 66 healthy subjects were administered clopidogrel (300 mg loading dose followed by 75 mg per day) alone and with oral pantoprazole (80 mg at the same time as clopidogrel) for 5 days. On Day 5, the mean AUC of the active metabolite of clopidogrel was reduced by approximately 14% (geometric mean ratio was 86%, with 90% CI of 79 to 93%) when pantoprazole sodium was coadministered with clopidogrel as compared to clopidogrel administered alone. Pharmacodynamic parameters were also measured and demonstrated that the change in inhibition of platelet aggregation (induced by 5 micromolar ADP) was correlated with the change in the exposure to clopidogrel active metabolite. The clinical significance of this finding is not clear.

Mycophenolate Mofetil (MMF)

Administration of oral pantoprazole 40 mg twice daily for 4 days and a single 1000 mg dose of MMF approximately one hour after the last dose of pantoprazole to 12 healthy subjects in a cross-over study resulted in a 57% reduction in the Cmax and 27% reduction in the AUC of MPA. Transplant patients receiving approximately 2000 mg per day of MMF (n=12) were compared to transplant patients receiving approximately the same dose of MMF and oral pantoprazole 40 mg per day (n=21). There was a 78% reduction in the Cmax and a 45% reduction in the AUC of MPA in patients receiving both pantoprazole and MMF [see Drug Interactions (7)].

Other Drugs

In vivo studies also suggest that pantoprazole does not significantly affect the kinetics of other drugs (cisapride, theophylline, diazepam [and its active metabolite, desmethyldiazepam], phenytoin, metoprolol, nifedipine, carbamazepine, midazolam, clarithromycin, diclofenac, naproxen, piroxicam and oral contraceptives [levonorgestrel/ethinyl estradiol]). In other in vivo studies, digoxin, ethanol, glyburide, antipyrine, caffeine, metronidazole, and amoxicillin had no clinically relevant interactions with pantoprazole.

Although no significant drug-drug interactions have been observed in clinical studies, the potential for significant drug-drug interactions with more than once daily dosing with high doses of pantoprazole has not been studied in poor metabolizers or individuals who are hepatically impaired.

Antacids

There was also no interaction with concomitantly administered antacids.

12.5 Pharmacogenomics

CYP2C19 displays a known genetic polymorphism due to its deficiency in some subpopulations (e.g., approximately 3% of Caucasians and African-Americans and 17% to 23% of Asians are poor metabolizers). Although these subpopulations of pantoprazole poor metabolizers have elimination half-life values of 3.5 to 10.0 hours in adults, they still have minimal accumulation (23% or less) with once-daily dosing. For adult patients who are CYP2C19 poor metabolizers, no dosage adjustment is needed.

Similar to adults, pediatric patients who have the poor metabolizer genotype of CYP2C19 (CYP2C19 *2/*2) exhibited greater than a 6-fold increase in AUC compared to pediatric extensive (CYP2C19 *1/*1) and intermediate (CYP2C19 *1/*x) metabolizers. Poor metabolizers exhibited approximately 10-fold lower apparent oral clearance compared to extensive metabolizers.

13 NONCLINICAL TOXICOLOGY

13.1 Carcinogenesis, Mutagenesis, Impairment of Fertility

In a 24-month carcinogenicity study, Sprague-Dawley rats were treated orally with pantoprazole doses of 0.5 to 200 mg/kg/day, about 0.1 to 40 times the exposure on a body surface area basis of a 50-kg person dosed at 40 mg/day. In the gastric fundus, treatment with 0.5 to 200 mg/kg/day produced enterochromaffin-like (ECL) cell hyperplasia and benign and malignant neuroendocrine cell tumors in a dose-related manner. In the forestomach, treatment with 50 and 200 mg/kg/day (about 10 and 40 times the recommended human dose on a body surface area basis) produced benign squamous cell papillomas and malignant squamous cell carcinomas. Rare gastrointestinal tumors associated with pantoprazole treatment included an adenocarcinoma of the duodenum with 50 mg/kg/day and benign polyps and adenocarcinomas of the gastric fundus with 200 mg/kg/day. In the liver, treatment with 0.5 to 200 mg/kg/day produced dose-related increases in the incidences of hepatocellular adenomas and carcinomas. In the thyroid gland, treatment with 200 mg/kg/day produced increased incidences of follicular cell adenomas and carcinomas for both male and female rats.

In a 24-month carcinogenicity study, Fischer 344 rats were treated orally with pantoprazole doses of 5 to 50 mg/kg/day, approximately 1 to 10 times the recommended human dose based on body surface area. In the gastric fundus, treatment with 5 to 50 mg/kg/day produced enterochromaffin-like (ECL) cell hyperplasia and benign and malignant neuroendocrine cell tumors. Dose selection for this study may not have been adequate to comprehensively evaluate the carcinogenic potential of pantoprazole.

In a 24-month carcinogenicity study, B6C3F1 mice were treated orally with pantoprazole doses of 5 to 150 mg/kg/day, 0.5 to 15 times the recommended human dose based on body surface area. In the liver, treatment with 150 mg/kg/day produced increased incidences of hepatocellular adenomas and carcinomas in female mice. Treatment with 5 to 150 mg/kg/day also produced gastric fundic ECL cell hyperplasia.

A 26-week p53 +/- transgenic mouse carcinogenicity study was not positive.

Pantoprazole was positive in the in vitro human lymphocyte chromosomal aberration assays, in one of two mouse micronucleus tests for clastogenic effects, and in the in vitro Chinese hamster ovarian cell/HGPRT forward mutation assay for mutagenic effects. Equivocal results were observed in the in vivo rat liver DNA covalent binding assay. Pantoprazole was negative in the in vitro Ames mutation assay, the in vitro unscheduled DNA synthesis (UDS) assay with rat hepatocytes, the in vitro AS52/GPT mammalian cell-forward gene mutation assay, the in vitro thymidine kinase mutation test with mouse lymphoma L5178Y cells, and the in vivo rat bone marrow cell chromosomal aberration assay.

There were no effects on fertility or reproductive performance when pantoprazole was given at oral doses up to 500 mg/kg/day in male rats (98 times the recommended human dose based on body surface area) and 450 mg/kg/day in female rats (88 times the recommended human dose based on body surface area).

14 CLINICAL STUDIES

14.1 Gastroesophageal Reflux Disease (GERD) Associated with a History of Erosive Esophagitis

A multicenter, double-blind, two-period placebo-controlled study was conducted to assess the ability of pantoprazole sodium injection to maintain gastric acid suppression in patients switched from pantoprazole delayed-release tablets to pantoprazole sodium injection GERD patients (n=65, 26 to 64 years; 35 female; 9 Black, 11 Hispanic, 44 White, 1 other) with a history of EE were randomized to receive either 20 or 40 mg of oral pantoprazole once per day for 10 days (period 1), and then were switched in period 2 to either daily pantoprazole sodium injection or placebo for 7 days, matching their respective dose level from period 1. Patients were administered all test medication with a light meal. Maximum acid output (MAO) and basal acid output (BAO) were determined 24 hours following the last day of oral medication (day 10), the first day (day 1) of intravenous administration and the last day of intravenous administration (day 7). MAO was estimated from a 1 hour continuous collection of gastric contents following subcutaneous injection of 6.0 mcg/kg of pentagastrin.

This study demonstrated that, after 10 days of repeated oral administration followed by 7 days of intravenous administration, the oral and intravenous dosage forms of pantoprazole 40 mg are similar in their ability to suppress MAO and BAO in patients with GERD and a history of EE (see Table 4). Also, patients on oral pantoprazole who were switched to intravenous placebo experienced a significant increase in acid output within 48 hours of their last oral dose (see Table 4). However, at 48 hours after their last oral dose, patients treated with pantoprazole sodium injection had a significantly lower mean basal acid output (see Table 4) than those treated with placebo.

Table 4. Antisecretory Effects (mEq/h) of 40 mg Pantoprazole Sodium Injection and 40 mg Pantoprazole Delayed-Release Tablets in GERD Patients with a History of EE
Parameter | Pantoprazole Delayed-Release Tablets DAY 10 | Pantoprazole Sodium for Injection DAY 7 | Intravenous Placebo DAY 7
Mean maximum acid output | 6.49; n=30 | 6.62; n=23 | 29.19 [p<0.0001 Significantly different from pantoprazole sodium injection]; n=7
Mean basal acid output | 0.80; n=30 | 0.53; n=23 | 4.14; n=7

To evaluate the effectiveness of pantoprazole sodium injection as an initial treatment to suppress gastric acid secretion, two studies were conducted.

Study 1 was a multicenter, double-blind, placebo-controlled, study of the pharmacodynamic effects of pantoprazole sodium injection and pantoprazole delayed-release tablets. Patients with GERD and a history of EE (n=78, 20 to 67 years; 39 females; 7 Black, 19 Hispanic, 52 White) were randomized to receive either 40 mg pantoprazole sodium injection, 40 mg pantoprazole delayed-release tablets, or placebo once daily for 7 days. Following an overnight fast, test medication was administered and patients were given a light meal within 15 minutes. MAO and BAO were determined 24 hours following the last day of study medication. MAO was estimated from a 1 hour continuous collection of gastric contents following subcutaneous injection of 6.0 mcg/kg of pentagastrin to stimulate acid secretion. This study demonstrated that, after treatment for 7 days, patients treated with pantoprazole sodium injection had a significantly lower MAO and BAO than those treated with placebo (p<0.001), and results were comparable to those of patients treated with pantoprazole delayed-release tablets (see Table 5).

Table 5. Antisecretory Effects (mEq/h) of Initial Treatment with 40 mg Pantoprazole Sodium Injection and 40 mg Pantoprazole Delayed-Release Tablets in GERD Patients with a History of EE
Parameter | Pantoprazole Sodium for Injection DAY 7 | Pantoprazole Delayed-Release Tablets DAY 7 | Placebo DAY 7
Maximum acid output (mean ± SD) | 8.4 ± 5.9; n=25 | 6.3 ± 6.6; n=22 | 20.9 ± 14.5 [p<0.001 Significantly different from pantoprazole sodium injection]; n=24
Basal acid output (mean ± SD) | 0.4 ± 0.5; n=25 | 0.6 ± 0.8; n=22 | 2.8 ± 3.0; n=23

Study 2 was a single-center, double-blind, parallel-group study to compare the clinical effects of pantoprazole sodium injection and pantoprazole delayed-release tablets. Patients (n=45, median age 56 years, 21 males and 24 females) with acute endoscopically proven reflux esophagitis (Savary/Miller Stage II or III) with at least 1 of 3 symptoms typical for reflux esophagitis (acid eructation, heartburn, or pain on swallowing) were randomized to receive either 40 mg pantoprazole sodium injection or 40 mg pantoprazole delayed-release tablets once daily for 5 days. After the initial 5 days, all patients were treated with 40 mg oral pantoprazole daily to complete a total of 8 weeks of treatment. Symptom relief was assessed by calculating the daily mean of the sums of the average scores for these 3 symptoms and the daily mean of the average score for each of the symptoms separately. There was no significant difference in symptom relief between pantoprazole sodium injection and pantoprazole delayed-release tablets within the first 5 days. A repeat endoscopy after 8 weeks of treatment revealed that 20 out of 23 (87%) patients treated with pantoprazole sodium injection plus pantoprazole delayed-release tablets and 19 out of 22 (86%) of the patients treated with pantoprazole delayed-release tablets had endoscopically proven healing of their esophageal lesions.

Data comparing pantoprazole sodium injection to other PPIs (oral or intravenous) or H2-receptor antagonists (oral or intravenous) are limited, and therefore, are inadequate to support any conclusions regarding comparative efficacy.

14.2 Pathological Hypersecretion Associated with Zollinger-Ellison Syndrome

Two studies measured the pharmacodynamic effects of 6 day treatment with pantoprazole sodium injection in patients with ZE Syndrome (with and without multiple endocrine neoplasia type I). In one of these studies, an initial treatment with pantoprazole sodium injection in 21 patients (29 to 75 years; 8 female; 4 Black, 1 Hispanic, 16 White) reduced acid output to the target level (10 mEq/h or less) and significantly reduced H^+ concentration and the volume of gastric secretions; target levels were achieved within 45 minutes of drug administration.

In the other study of 14 patients (38 to 67 years; 5 female; 2 Black, 12 White) with ZE Syndrome, treatment was switched from an oral PPI to pantoprazole sodium injection. Pantoprazole sodium injection maintained or improved control of gastric acid secretion.

In both studies, total doses of 160 or 240 mg per day of pantoprazole sodium injection, administered in divided doses, maintained basal acid secretion below target levels in all patients. Target levels were 10 mEq/h in patients without prior gastric surgery, and 5 mEq/h in all patients with prior gastric acid-reducing surgery. Once gastric acid secretion was controlled, there was no evidence of tolerance during this 7 day study. Basal acid secretion was maintained below target levels for at least 24 hours in all patients and through the end of treatment in these studies (3 to 7 days) in all but 1 patient who required a dose adjustment guided by acid output measurements until acid control was achieved. In both studies, doses were adjusted to the individual patient need, but gastric acid secretion was controlled in greater than 80% of patients by a starting regimen of 80 mg every 12 hours.

16 HOW SUPPLIED/STORAGE AND HANDLING

Pantoprazole sodium in 0.9% sodium chloride injection is supplied as a frozen, premixed, iso-osmotic, sterile, nonpyrogenic single-dose solution packaged in GALAXY container. The single-dose GALAXY plastic containers are available as follows:

Code | NDC | Container | Size | Number of Containers/Carton
2G3571 | NDC 0338-9644-12 | GALAXY single-dose | 100 mL | 12 count of 40 mg/100 mL (0.4 mg/mL) GALAXY containers
2G3569 | NDC 0338-9646-24 | GALAXY single-dose | 50 mL | 24 count of 40 mg/50 mL (0.8 mg/mL) GALAXY containers
2G3581 | NDC 0338-9648-12 | GALAXY single-dose | 100 mL | 12 count of 80 mg/100 mL (0.8 mg/mL) GALAXY containers

Storage and Handling

Store frozen at or below -20°C /-4°F. Protect from light when stored frozen.

Handle frozen product containers with care. Product containers may be fragile in the frozen state. Storage conditions for the thawed solution are described in another section of the prescribing information. [see Dosage and Administration (2.3)].

17 PATIENT COUNSELING INFORMATION

Adverse Reactions

Advise patients to report to their healthcare provider if they experience any signs or symptoms consistent with:

- Injection Site Reactions [see Warnings and Precautions (5.2)]
- Potential for Exacerbation of Zinc Deficiency [see Warnings and Precautions (5.3)]
- Acute Tubulointerstitial Nephritis [see Contraindications (4), Warnings and Precautions (5.4)]
- Clostridium difficile-Associated Diarrhea [see Warnings and Precautions (5.5)]
- Bone Fracture [see Warnings and Precautions (5.6)]
- Severe Cutaneous Adverse Reactions [see Warnings and Precautions (5.7)]
- Cutaneous and Systemic Lupus Erythematosus [see Warnings and Precautions (5.8)]
- Hepatic Effects [see Warnings and Precautions (5.9)]
- Hypomagnesemia and Mineral Metabolism [see Warnings and Precautions (5.10)]

Drug Interactions

Instruct patients to inform their healthcare provider of any other medications they are currently taking, including rilpivirine-containing products [Contraindications (4)] and high dose methotrexate [Warnings and Precautions (5.14)].

Pregnancy

Advise a pregnant woman of the potential risk to a fetus. Advise females of reproductive potential to inform their healthcare provider of a known or suspected pregnancy [see Use in Specific Populations (8.1)].

This product’s labeling may have been updated. For the most recent prescribing information, please visit www.baxter.com.

Baxter logo

Baxter Healthcare Corporation
Deerfield, IL 60015 USA

Product of USA

Baxter and Galaxy are trademarks of Baxter International Inc. or its subsidiaries.

PACKAGE/LABEL PRINCIPAL DISPLAY PANEL

Container Label

NDC 0338-9644-12

40 mg
TOTAL

Pantoprazole Sodium
in 0.9% Sodium Chloride Injection

40 mg/100 mL (0.4 mg/mL)*

For Intravenous Infusion Only
100 mL Single-Dose GALAXY Container
Discard Unused Portion

Rx only
Sterile

*Each 100 mL contains: 40 mg of pantoprazole (equivalent to
45.1 mg of pantoprazole sodium USP); 1 mg edetate disodium, USP;
155 mg histidine, USP; 900 mg sodium chloride, USP; and water for
injection, USP.

Usual Dosage: See prescribing information.

Store frozen at or below -20°C /-4°F.

Thaw at room temperature 20-25°C (68 - 77°F) or under
refrigeration 2-8°C (36 - 46°F) and store thawed solution as follows:
- Refrigerated Storage: Use within 21 days
- Room Temperature Storage: Use within 48 hours

Protect from light when stored frozen or under refrigeration.

Do not force thaw. Do not refreeze the thawed solution.

Thawed solution is expected to range from colorless to yellow
over time.

Do not add supplemental medication or additives.

Baxter Logo
Baxter and Galaxy are trademarks of Baxter International Inc.
or its subsidiaries.
Baxter Healthcare Corporation, Deerfield, IL 60015 USA

Code 2G3571
PL 2040 Plastic
Product of USA
07-34-00-1222

BAR CODE
POSITION ONLY UPC-A

XXXXXXXXXXXX

Carton Label

Store frozen at or below -20°C /-4°F. Thaw at room temperature 20-25°C (68 - 77°F) or under refrigeration
2-8°C (36 - 46°F) and store thawed solution as follows:
- Refrigerated Storage: Use within 21 days
- Room Temperature Storage: Use within 48 hours

Protect from light when stored frozen or under refrigeration.

Do not force thaw. Do not refreeze the thawed solution.
Handle frozen product containers with care. Product containers may be fragile in the frozen state.

40 mg
TOTAL

Pantoprazole Sodium
in 0.9% Sodium Chloride Injection

40 mg/100 mL (0.4 mg/mL)*

Contains 6 units of Single-Dose bags.
Each bag contains 100 mL.
Store frozen at or below -20°C /-4°F.

Baxter Logo

Rx only

*FOR BAR CODE
POSITION ONLY

(01) 0000000000000 (10)XX000000
(21) 000000000000 (17)000000

NDC 0338-9644-12
Code 2G3571

*FOR BAR CODE POSITION ONLY

(01) XXXXXXXXXXXXXX

*Each 100 mL contains: 40 mg of pantoprazole (equivalent to 45.1 mg of pantoprazole sodium USP); 1 mg edetate
disodium, USP; 155 mg histidine, USP; 900 mg sodium chloride, USP; and water for injection, USP.

Usual Dosage: See prescribing information.

Baxter Healthcare Corporation, Deerfield, IL 60015 USA
PL 2040 Plastic 07-04-00-0582

Container Label

NDC 0338-9646-24

40 mg
TOTAL

Pantoprazole Sodium
in 0.9% Sodium Chloride Injection

40 mg/50 mL (0.8 mg/mL)*

For Intravenous Infusion Only
50 mL Single-Dose GALAXY Container
Discard Unused Portion

Rx only
Sterile

*Each 50 mL contains: 40 mg of pantoprazole (equivalent to 45.1 mg of
pantoprazole sodium USP); 1 mg edetate disodium, USP; 77.5 mg histidine, USP;
450 mg sodium chloride, USP; and water for injection, USP.
Usual Dosage: See prescribing information.
Store frozen at or below -20°C /-4°F.
Thaw at room temperature 20-25°C (68 - 77°F) or under refrigeration
2-8°C (36 - 46°F) and store thawed solution as follows:
- Refrigerated Storage: Use within 21 days
- Room Temperature Storage: Use within 48 hours
Protect from light when stored frozen or under refrigeration.
Do not force thaw. Do not refreeze the thawed solution.
Thawed solution is expected to range from colorless to yellow
over time.
Do not add supplemental medication or additives.

Baxter Logo
Baxter and Galaxy are trademarks of Baxter International Inc.
or its subsidiaries.
Baxter Healthcare Corporation, Deerfield, IL 60015 USA

Code 2G3569
PL 2040 Plastic
Product of USA
07-34-00-1221

*BAR CODE
FOR POSITION ONLY

(1) XXXXXXXXXXXXXX

Carton Label

Store frozen at or below -20°C /-4°F. Thaw at room temperature 20-25°C (68 - 77°F) or under refrigeration
2-8°C (36 - 46°F) and store thawed solution as follows:
- Refrigerated Storage: Use within 21 days
- Room Temperature Storage: Use within 48 hours

Protect from light when stored frozen or under refrigeration.

Do not force thaw. Do not refreeze the thawed solution.
Handle frozen product containers with care. Product containers may be fragile in the frozen state.

40 mg
TOTAL

Pantoprazole Sodium
in 0.9% Sodium Chloride Injection

40 mg/50 mL (0.8 mg/mL)*

Contains 12 units of Single-Dose bags.
Each bag contains 50 mL.
Store frozen at or below -20°C /-4°F.

Baxter Logo

Rx only

*FOR BAR CODE
POSITION ONLY

(01) 0000000000000 (10)XX000000
(21) 000000000000 (17)000000

NDC 0338-9646-24
Code 2G3571

*FOR BAR CODE POSITION ONLY

(01) XXXXXXXXXXXXXX

*Each 50 mL contains: 40 mg of pantoprazole (equivalent to 45.1 mg of pantoprazole sodium USP); 1 mg edetate
disodium, USP; 77.5 mg histidine, USP; 450 mg sodium chloride, USP; and water for injection, USP.

Usual Dosage: See prescribing information.

Baxter Healthcare Corporation, Deerfield, IL 60015 USA
PL 2040 Plastic 07-04-00-0581

Container Label

NDC 0338-9648-12

80 mg
TOTAL

Pantoprazole Sodium
in 0.9% Sodium Chloride Injection

80 mg/100 mL (0.8 mg/mL)*

For Intravenous Infusion Only
100 mL Single-Dose GALAXY Container
Discard Unused Portion

Rx only
Sterile

*Each 100 mL contains: 80 mg of pantoprazole (equivalent to
90.2 mg of pantoprazole sodium USP); 2 mg edetate disodium, USP;
155 mg histidine, USP; 900 mg sodium chloride, USP; and water for
injection, USP.

Usual Dosage: See prescribing information.

Store frozen at or below -20°C /-4°F.

Thaw at room temperature 20-25°C (68 - 77°F) or under
refrigeration 2-8°C (36 - 46°F) and store thawed solution as follows:
- Refrigerated Storage: Use within 21 days
- Room Temperature Storage: Use within 48 hours

Protect from light when stored frozen or under refrigeration.

Do not force thaw. Do not refreeze the thawed solution.

Thawed solution is expected to range from colorless to yellow
over time.

Do not add supplemental medication or additives.

Baxter Logo
Baxter and Galaxy are trademarks of Baxter International Inc.
or its subsidiaries.
Baxter Healthcare Corporation, Deerfield, IL 60015 USA

Code 2G3581
PL 2040 Plastic
Product of USA
07-34-00-1223

BAR CODE
POSITION ONLY UPC-A

XXXXXXXXXXXX

Carton Label

Store frozen at or below -20°C /-4°F. Thaw at room temperature 20-25°C (68 - 77°F) or under refrigeration
2-8°C (36 - 46°F) and store thawed solution as follows:
- Refrigerated Storage: Use within 21 days
- Room Temperature Storage: Use within 48 hours

Protect from light when stored frozen or under refrigeration.

Do not force thaw. Do not refreeze the thawed solution.
Handle frozen product containers with care. Product containers may be fragile in the frozen state.

80 mg
TOTAL

Pantoprazole Sodium
in 0.9% Sodium Chloride Injection

80 mg/100 mL (0.8 mg/mL)*

Contains 6 units of Single-Dose bags.
Each bag contains 100 mL.
Store frozen at or below -20°C /-4°F.

Baxter Logo

Rx only

*FOR BAR CODE
POSITION ONLY

(01) 0000000000000 (10)XX000000
(21) 000000000000 (17)000000

NDC 0338-9648-12
Code 2G3581

*FOR BAR CODE POSITION ONLY

(01) XXXXXXXXXXXXXX

*Each 100 mL contains: 80 mg of pantoprazole (equivalent to 90.2 mg of pantoprazole sodium USP); 2 mg edetate
disodium, USP; 155 mg histidine, USP; 900 mg sodium chloride, USP; and water for injection, USP.

Usual Dosage: See prescribing information.

Baxter Healthcare Corporation, Deerfield, IL 60015 USA
PL 2040 Plastic 07-04-00-0583